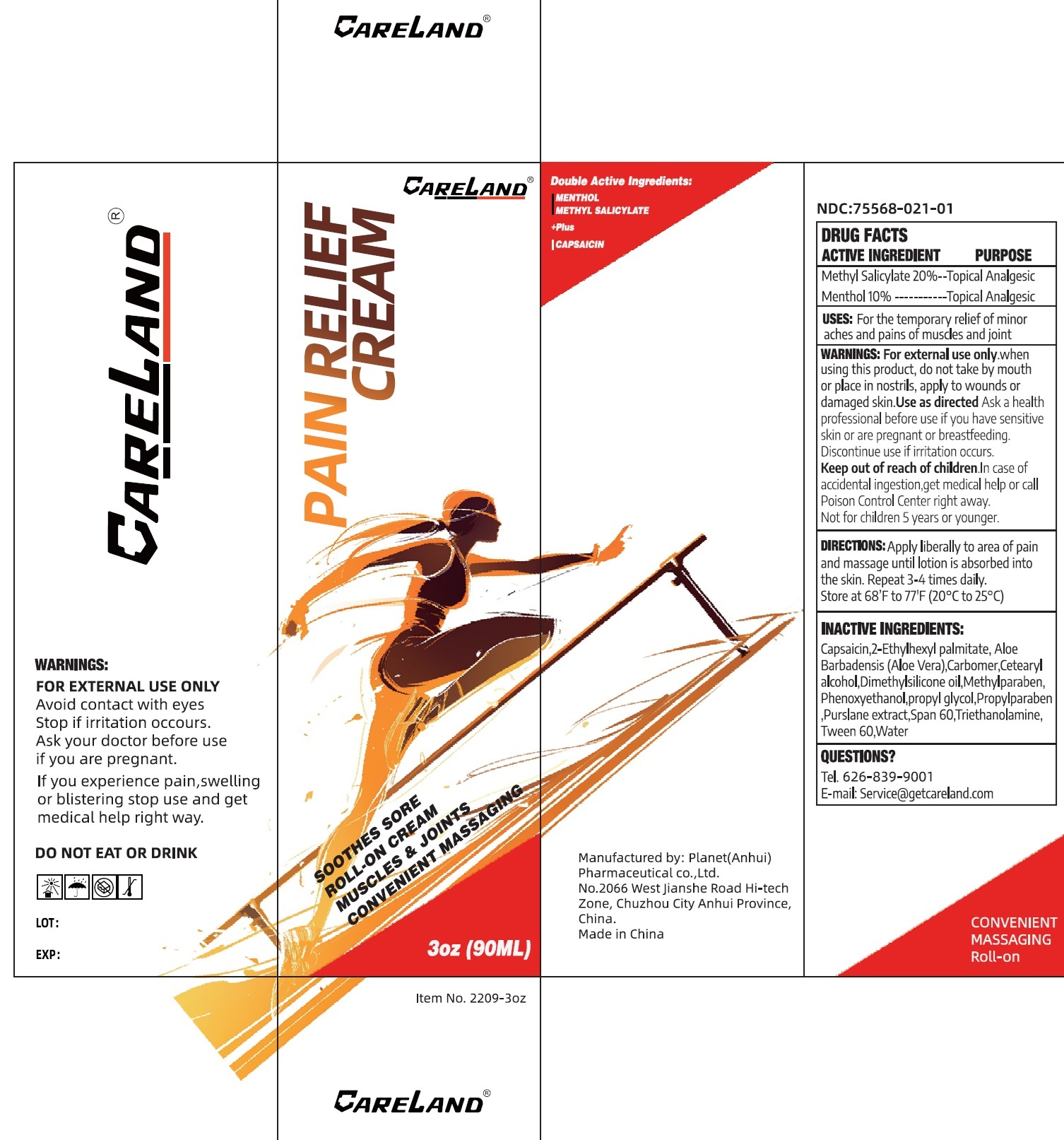 DRUG LABEL: Careland Pain Relief
NDC: 75568-021 | Form: CREAM
Manufacturer: Planet (Anhui) Pharmaceutical Co., Ltd.
Category: otc | Type: HUMAN OTC DRUG LABEL
Date: 20250728

ACTIVE INGREDIENTS: METHYL SALICYLATE 200 mg/1 mL; MENTHOL 100 mg/1 mL
INACTIVE INGREDIENTS: CAPSAICIN; ETHYLHEXYL PALMITATE; ALOE VERA LEAF; CARBOMER HOMOPOLYMER, UNSPECIFIED TYPE; CETOSTEARYL ALCOHOL; DIMETHICONE; METHYLPARABEN; PHENOXYETHANOL; PROPYLPARABEN; SORBITAN MONOSTEARATE; TROLAMINE; POLYSORBATE 60; WATER

Careland Pain Relief Cream

ACTIVE INGREDIENT

Methyl Salicylate 20%

Menthol 10%

PURPOSE

Topical Analgesic

USES:

For the temporary relief of minor aches and pains of muscles and joint

WARNINGS:

For external use only.

When using this product,

do not take by mouth or place in nostrils, apply to wounds or damaged skin. Use as directed

Ask a health professional before use

if you have sensitive skin or are pregnant or breastfeeding. Discontinue use if irritation occurs.

Keep out of reach of children.

In case of accidental ingestion,get medical help or call Poison Control Center right away. Not for children 5 years or younger.

DIRECTIONS:

Apply liberally to area of pain and massage until lotion is absorbed into the skin. Repeat 3-4 times daily. Store at 68'F to 77'F (20ºC to 25ºC)

INACTIVE INGREDIENTS:

Capsaicin,2-Ethylhexyl palmitate, Aloe barbadensis (Aloe Vera),Carbomer,Cetearyl alcohol,Dimethylsilicone oil,Methylparaben, Phenoxyethanol,propyl glycol,Propylparaben,Purslane extract,Span 60,Triethanolamine,Tween 60,Water

QUESTIONS?

Tel. 626-839-9001

E-mail: Service@getcareland.com